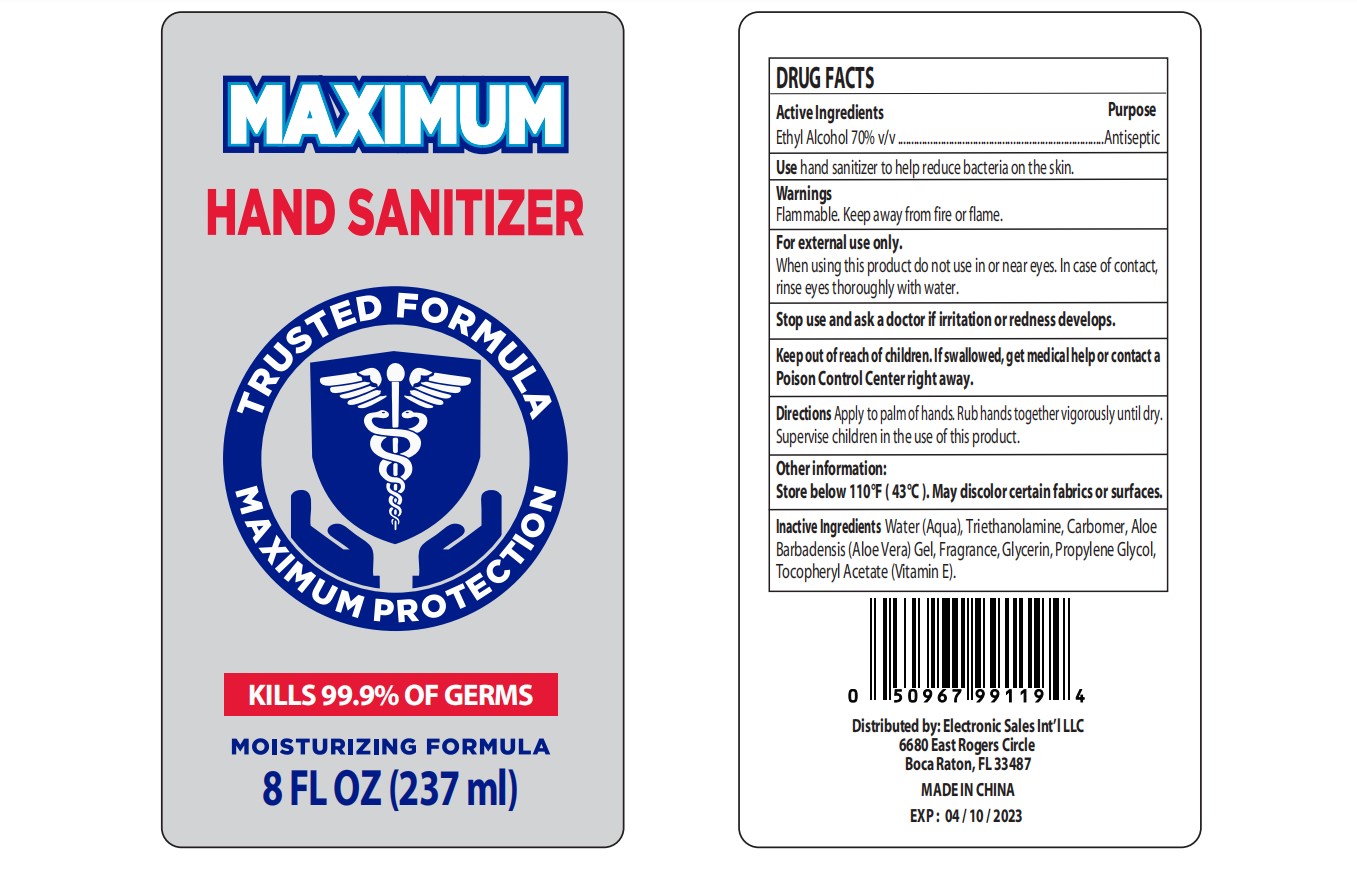 DRUG LABEL: Maximum Hand Sanitizer
NDC: 76114-003 | Form: SOLUTION
Manufacturer: Zhejiang Aidi Cosmetics Co., Ltd
Category: otc | Type: HUMAN OTC DRUG LABEL
Date: 20200424

ACTIVE INGREDIENTS: ALCOHOL 70 mL/100 mL
INACTIVE INGREDIENTS: GLYCERIN; WATER; CARBOMER 934; PROPYLENE GLYCOL; ALPHA-TOCOPHEROL ACETATE; TRIETHANOLAMINE SULFATE; ALOE VERA WHOLE

NA

Active Ingredient(s)

Ethyl Alcohol 70% v/v

Purpose

Antiseptic

Use

Hand sanitizer to help reduce bacteria on the skin

Warnings

Flammable. Keep away from fire or flame

For external use only.

When using this product do not use in or near the eyes. In case of contact with eyes, rinse eyes thoroughly with water.

Stop use and ask a doctor if irritation or redness develops

Keep out of reach of children. If swallowed, get medical help or contact a Poison Control Center right away.

Directions

Appply to palm of hands. Rub hands together vigorously untill dry.

Supervise chirldren in the use of this product.

Other information

Do not store above 110F (43C)

May discolor certain fabrics or surfaces

Inactive ingredients

Water, triethanolamine, carbomer, aloe barbadensis (Aloe vera) gel, fragrance, propylene glycol, glycerin, tocopheryl acetate (Vitamin E)